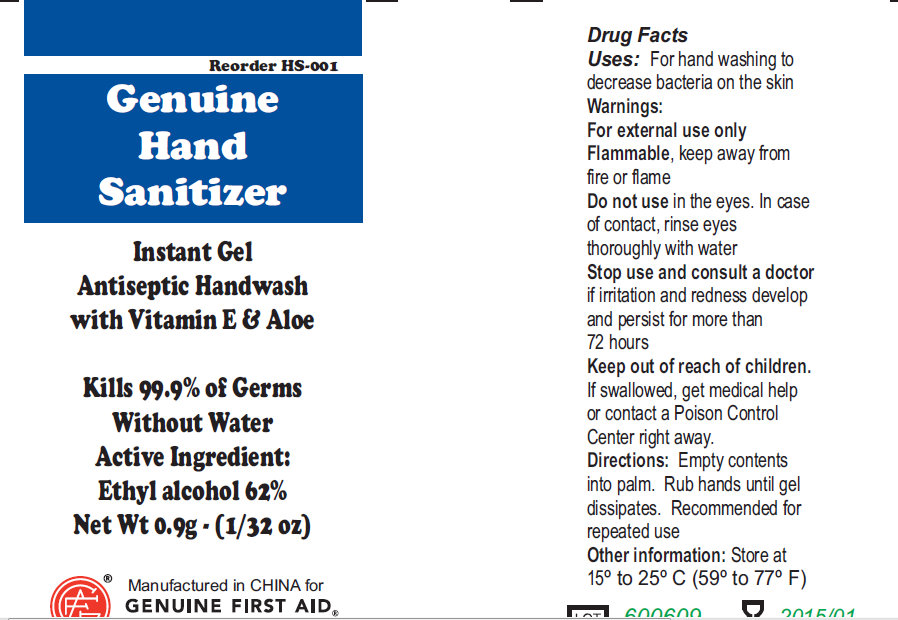 DRUG LABEL: Genuine Hand Sanitizer

NDC: 52124-0006 | Form: GEL
Manufacturer: Genuine First Aid LLC
Category: otc | Type: HUMAN OTC DRUG LABEL
Date: 20191205

ACTIVE INGREDIENTS: ALCOHOL 62 g/100 g
INACTIVE INGREDIENTS: PROPYLENE GLYCOL; TITANIUM DIOXIDE; WATER

Genuine Hand Sanitizer

Active Ingredient

Ethyl Alcohol 62%

Purpose

Antimicrobial

Uses

For handwashing to decrease bacteria on the skin.

Warnings

For external use only.

Flammable

Do not use

in the eyes. In case of contact, rinse eyes thoroughly with water.

Stop use and consult a doctor

if irritation and redness develop and persist for more than 72 hours

Directions

Empty contents into palm. Rub hands until gel dissipates. Recommended for repeated use.

Inactive Ingredients

Propylene glycol, carbomer, titanium dioxide, purified water

Keep out of reach of children

If swallowed, get medical help or contact a Poison Control Center right away.

PACKAGE LABEL

Genuine Hand Sanitizer

Instant Gel

Antiseptic Handwash

with Vitamin E and Aloe

Kills 99.9 percent of germs

Without Water

Active Ingredient:

Ethyl Alcohol 62 percent
Net Wt 0.9g (1/32 oz)
Manufactured in China For
Genuine First Aid.